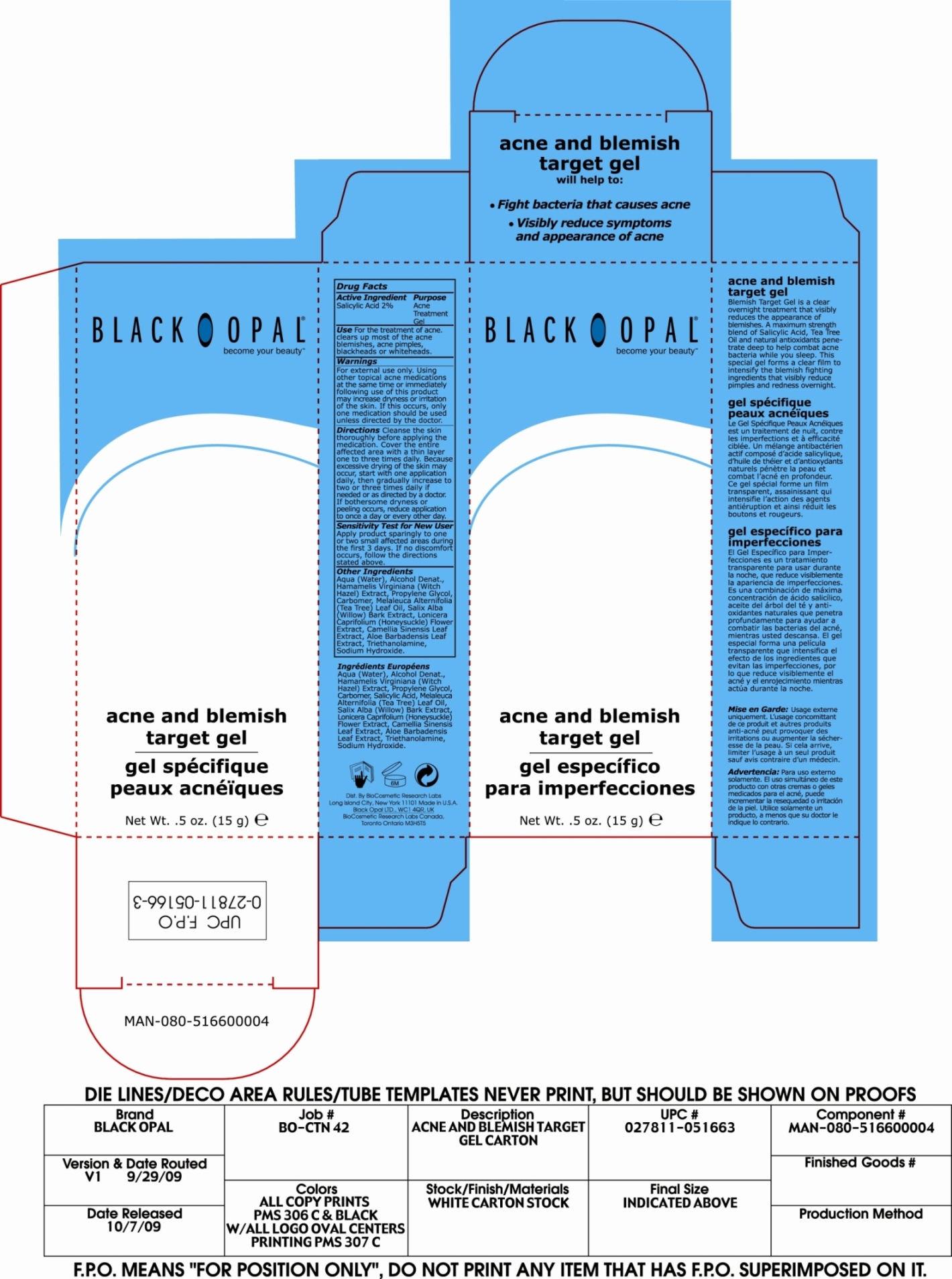 DRUG LABEL: Acne and Blemish Target
NDC: 59735-302 | Form: GEL
Manufacturer: Biocosmetics Research Labs
Category: otc | Type: HUMAN OTC DRUG LABEL
Date: 20030213

ACTIVE INGREDIENTS: Salicylic Acid 2 g/100 g

Acne and Blemish Target Gel

Active Ingredient

Salicylic Acid 2%

Purpose
Acne Treatment Gel

INDICATIONS AND USAGE

Use For the treatment of acne. Clears up most of the acne blemishes, acne pimples, blackheads or whiteheads.

Warnings

For external use only.

Using other topical acne medications at the same time or immediately following the use of this product may increase dryness or irritation of the skin. If this occurs, only one medication should be used unless directed by a doctor.

Directions:

Cleanse the skin thoroughly before applying the medication. Cover the entire affected area with a thin layer one to three times daily. Because excessive drying of the skin may occur start with one application daily, then gradually increase to two or three times daily if needed or as directed by a doctor. If bothersome dryness or peeling occurs, reduce application to once a day or every other day.

PRECAUTIONS

Sensitivity test for new user:

Apply product sparingly to one or two small affected areas during the first three days. If no discomfort occurs, follow the directions stated above.

Inactive Ingredients:

Water (Aqua), Alcohol Denat., Hamamelis Virginiana (Witch Hazel) Extract, Propylene Glycol, Carbomer, Melaleuca Alternifolia (Tea Tree) Leaf Oil, Salix Alba (Willow) Bark Extract, Lonicera Caprifolium (Honeysuckle) Flower Extract, Camellia Sinensis Leaf Extract, Aloe Barbadensis Leaf Extract, Triethanolamine, Sodium Hydroxide.